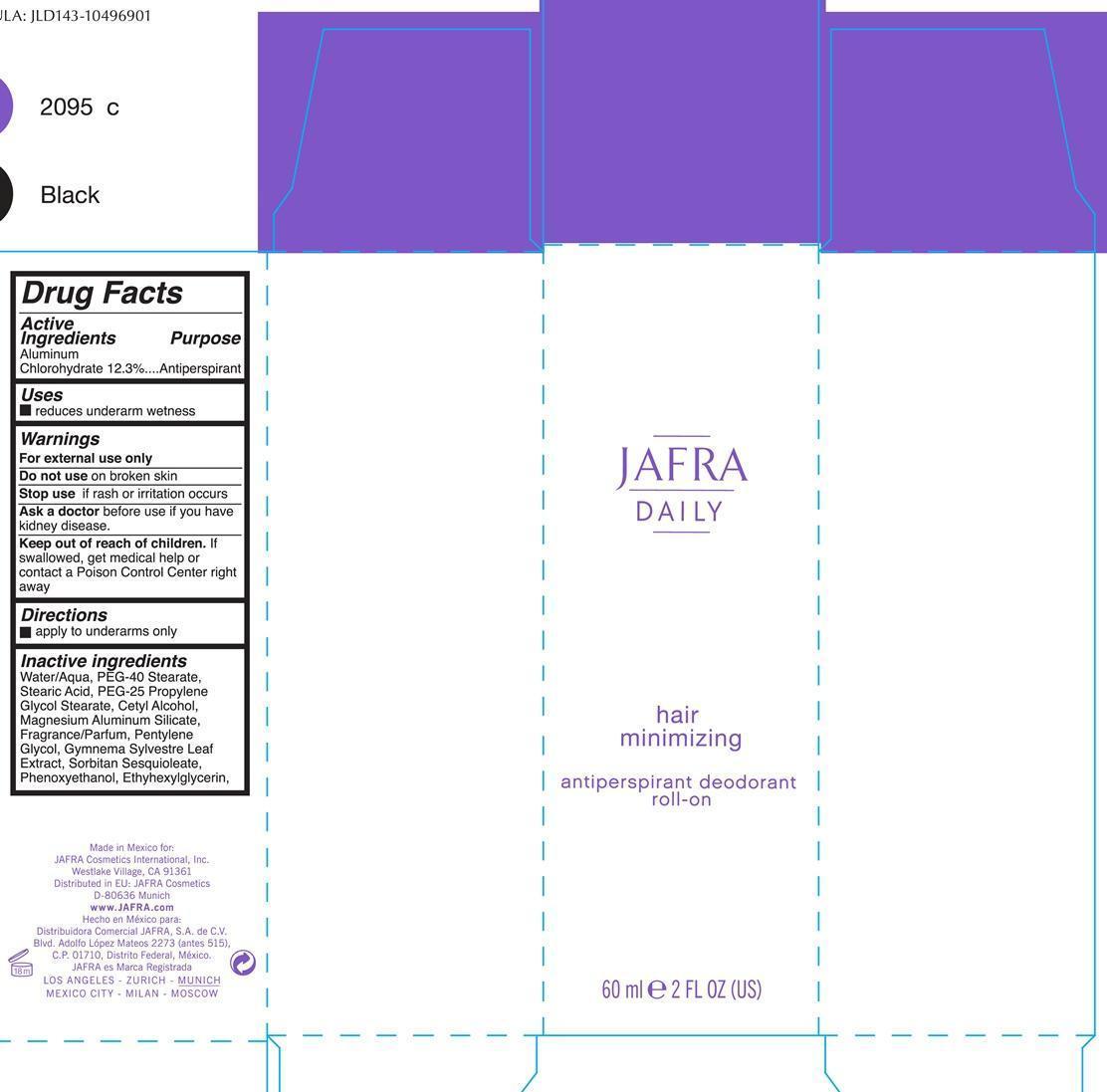 DRUG LABEL: hair minimizing antiperspirant deodorant roll-on
NDC: 68828-200 | Form: LIQUID
Manufacturer: Jafra cosmetics International
Category: otc | Type: HUMAN OTC DRUG LABEL
Date: 20190405

ACTIVE INGREDIENTS: ALUMINUM CHLOROHYDRATE 100 g/100 mL
INACTIVE INGREDIENTS: WATER; PEG-40 STEARATE; STEARIC ACID; PEG-25 PROPYLENE GLYCOL STEARATE; GLYCOL STEARATE; CETYL ALCOHOL; MAGNESIUM ALUMINUM SILICATE; PENTYLENE GLYCOL; GYMNEMA SYLVESTRE LEAF; SORBITAN SESQUIOLEATE; PHENOXYETHANOL; ETHYLHEXYLGLYCERIN

Hair Minimizing Antiperspirant Roll on

Active ingredients Purpose
Aluminum Chlorohydrate 12.3% Antiperspirant

Uses

reduces underarm wetness

Keep out of reach of children. If swallowed, get medical help or contact a Poison Control Center right away

Stop use if rash or irritation occurs

Warnings

For External Use only

Do not use on broken skin

Ask a doctor before use if you have kidney disease

Directions

apply to underarms only

INACTIVE INGREDIENT

Water/Aqua, PEG-40 Stearate, Stearic Acid, PEG-25 Propylene Glycol Stearate, Cetyl Alcohol, Magnesium Aluminum Silicate, Fragrance/Parfum, pentylene Glycol, Gymnema Sylvestre Leaf Extract, Sorbitan Sesquioleate, Phenoxyethanol, Ethylhexylglycerin.

PACKAGE LABEL

Jafra

Daily

hair minimizing

antiperspirant deodorant roll-on
60ml 2 FL OZ